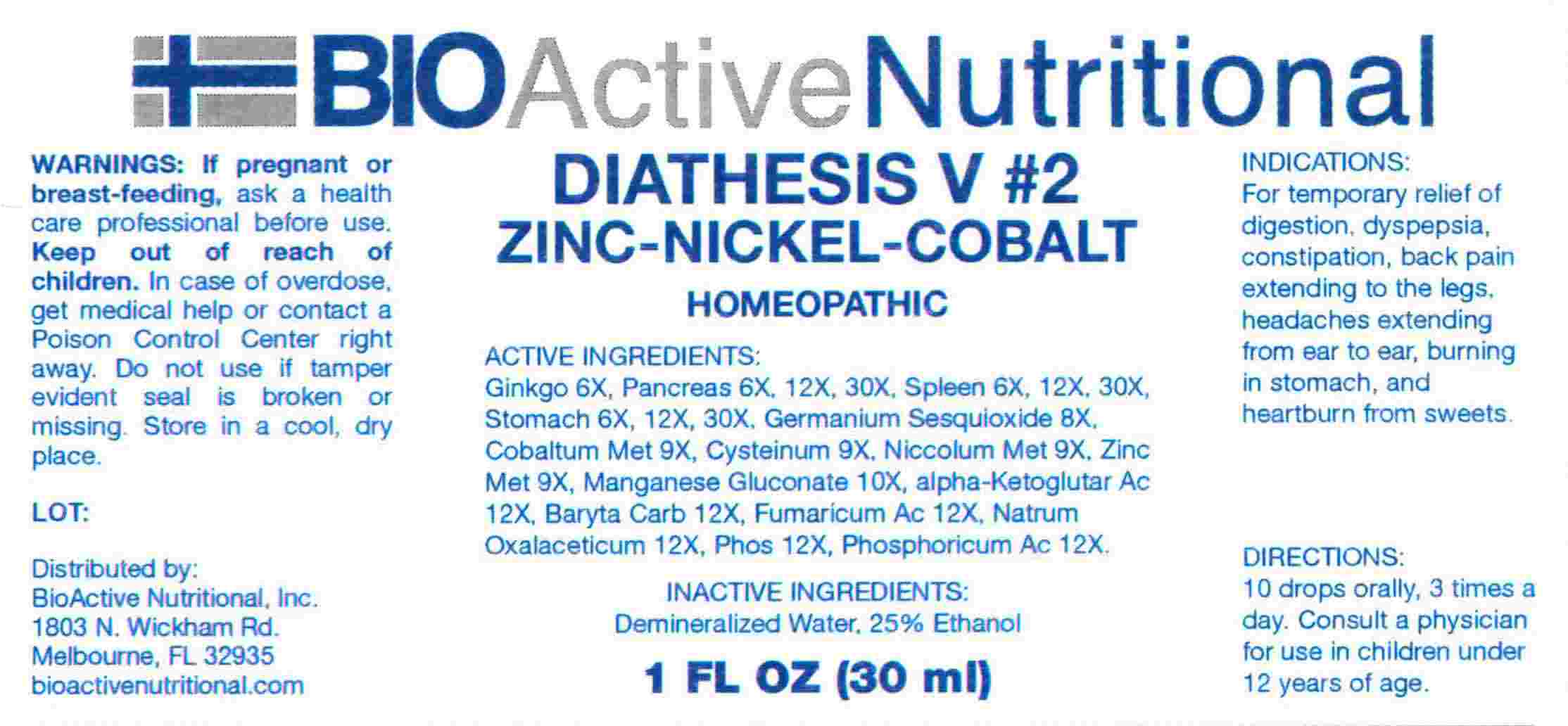 DRUG LABEL: Diathesis V 2
NDC: 43857-0638 | Form: LIQUID
Manufacturer: BioActive Nutritional, Inc.
Category: homeopathic | Type: HUMAN OTC DRUG LABEL
Date: 20240213

ACTIVE INGREDIENTS: GINKGO 6 [hp_X]/1 mL; SUS SCROFA PANCREAS 6 [hp_X]/1 mL; SUS SCROFA SPLEEN 6 [hp_X]/1 mL; SUS SCROFA STOMACH 6 [hp_X]/1 mL; GERMANIUM SESQUIOXIDE 8 [hp_X]/1 mL; COBALT 9 [hp_X]/1 mL; CYSTEINE 9 [hp_X]/1 mL; NICKEL 9 [hp_X]/1 mL; ZINC 9 [hp_X]/1 mL; MANGANESE GLUCONATE, UNSPECIFIED FORM 10 [hp_X]/1 mL; OXOGLURIC ACID 12 [hp_X]/1 mL; BARIUM CARBONATE 12 [hp_X]/1 mL; FUMARIC ACID 12 [hp_X]/1 mL; SODIUM DIETHYL OXALACETATE 12 [hp_X]/1 mL; PHOSPHORIC ACID 12 [hp_X]/1 mL; PHOSPHORUS 12 [hp_X]/1 mL
INACTIVE INGREDIENTS: WATER; ALCOHOL

DRUG FACTS:

ACTIVE INGREDIENTS:

Ginkgo Biloba 6X, Pancreas 6X, 12X, 30X, Spleen 6X, 12X, 30X, Stomach 6X, 12X, 30X, Germanium Sesquioxide 8X, Cobaltum Metallicum 9X, Cysteinum 9X, Niccolum Metallicum 9X, Zincum Metallicum 9X, Manganese Gluconate 10, Alpha-Ketoglutaricum Acidum 12X, Baryta Carbonica 12X, Fumaricum Acidum 12X, Natrum Oxalaceticum 12X, Phosphoricum Acidum 12X, Phosphorus 12X.

PURPOSE:

For temporary relief of digestion, dyspepsia, constipation, back pain extending to the legs, headaches extending from ear to ear, burning in stomach, and heartburn from sweets.

WARNINGS:

If pregnant or breast-feeding, ask a health care professional before use.

Keep out of reach of children. In case of overdose, get medical help or contact a Poison Control Center right away.

Do not use if tamper evident seal is broken or missing.

Store in cool, dry place.

KEEP OUT OF REACH OF CHILDREN:

In case of overdose, get medical help or contact a Poison Control Center right away.

DIRECTIONS:

10 drops orally, 3 times a day. Consult a physician for use in children under 12 years of age.

INDICATIONS:

For temporary relief of digestion, dyspepsia, constipation, back pain extending to the legs, headaches extending from ear to ear, burning in stomach, and heartburn from sweets.

INACTIVE INGREDIENTS:

Demineralized Water, 25% Ethanol

QUESTIONS:

Distributed by:
BioActive Nutritional, Inc.
1803 N. Wickham Rd.
Melbourne, FL 32935
bioactivenutritional.com

PACKAGE LABEL DISPLAY:

BIOActive Nutritional

DIATHESIS V #2

ZINC-NICKEL-COBALT

HOMEOPATHIC

1 FL OZ (30 ml)